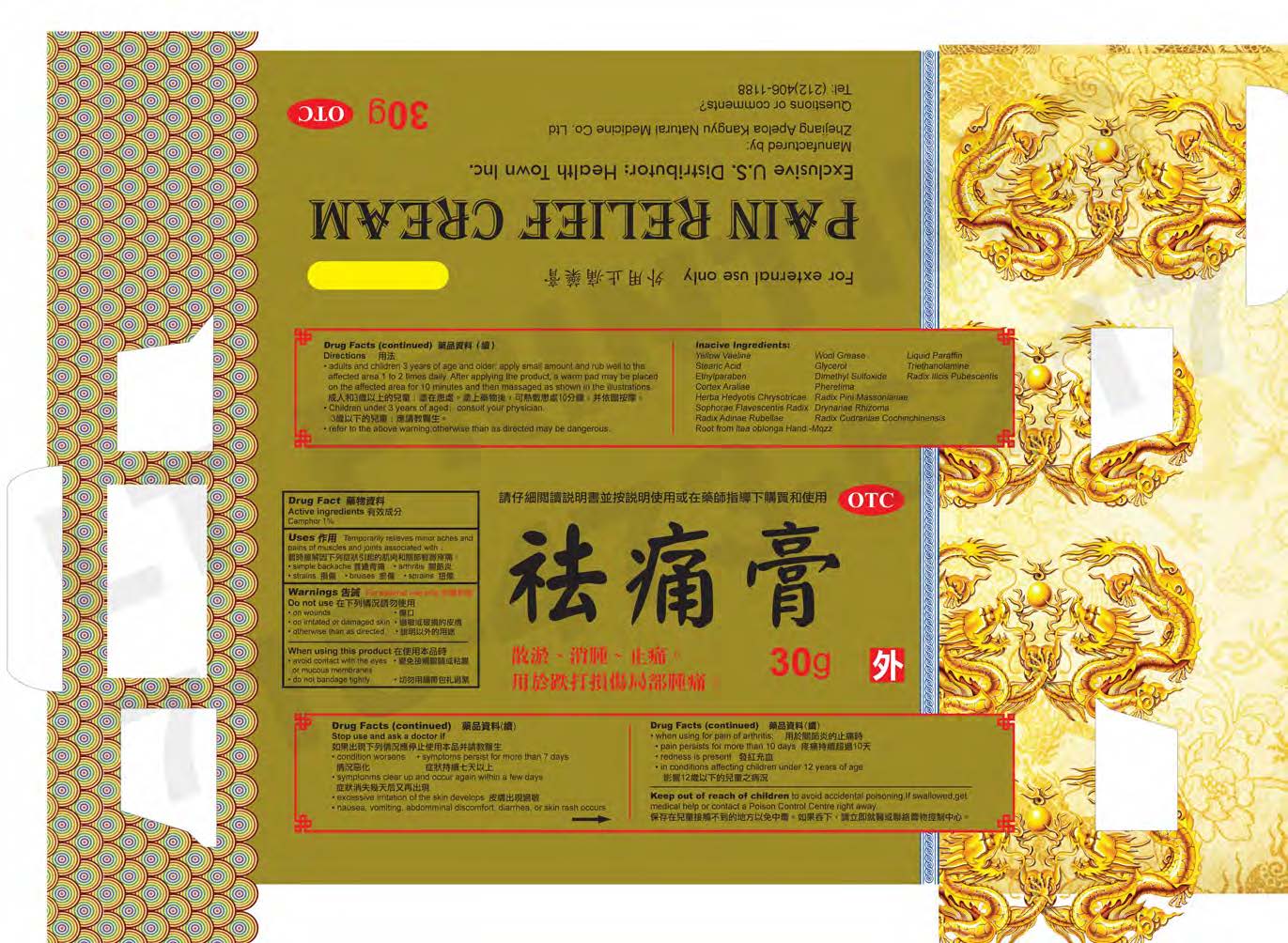 DRUG LABEL: Pain Relief Cream
NDC: 70576-001 | Form: CREAM
Manufacturer: Health Town Inc
Category: otc | Type: HUMAN OTC DRUG LABEL
Date: 20160324

ACTIVE INGREDIENTS: CAMPHOR (NATURAL) 1 g/100 g
INACTIVE INGREDIENTS: MINERAL OIL; ETHYLPARABEN; TROLAMINE; ILEX PUBESCENS ROOT; PHERETIMA ASPERGILLUM; STEARIC ACID; ARALIA CHINENSIS WHOLE; OLDENLANDIA DIFFUSA; PINUS MASSONIANA LEAF; AMPELOPSIS GLANDULOSA VAR. BREVIPEDUNCULATA FRUIT; GLYCERIN; DIMETHYL SULFOXIDE; LANOLIN; MACLURA COCHINCHINENSIS ROOT; PETROLATUM; SOPHORA FLAVESCENS ROOT; DRYNARIA FORTUNEI ROOT; ADINA RUBELLA ROOT

ACTIVE INGREDIENT

Camphor 1%

PURPOSE

External Analgesic

Topical Analgesic

Pain relieving cream

INDICATIONS AND USAGE

Temporarily relieves minor aches and pains of muscles and joints associate with:

-simple backache

-arthritis

-strains

-bruises

-spains

KEEP OUT OF REACH OF CHILDREN

Children under 2 years of age: consult a doctor.

WARNINGS

For extenal use only

Do not use:

-on wounds

-on irritated or damaged skin

-otherwise than as directed

When using this product:

-avoid contact with the eyes or mucous membranes

-do not bandage tightly

DOSAGE AND ADMINISTRATION

-adults and children 3 years of age and older: apply 3 or 4 drops of medicate oil to the affecte area 1 to 2 times daily. After applying the product, a warm pad may be placed on the affected area for 10 minutes and ten massaged as shown in the illustrations.

-Children under 3 years of age, consult your physician

-refer to the above warning; otherwise than as directed may be dangerous

INACTIVE INGREDIENT

Yellow Vaseline

Wool Grease

Liquid Paraffin

Stearic Acid

Glycerol

Triethanolamine

Ethylparaben

Dimethyl Sulfoxide

Radix Illcis Pubescentis

Cortex Araliae

Pheretima

Herba Hedyotis Chrysotricae

Radix Pini Massonianae

Sophorae Flavescentis Radix

Drynariae Rhizoma

Radix Adinae Rubellae

Radix Cudraniae Cochinchinensis

Root from Itea Oblonga Hand.-Mazz

Root from Syzygium Grijsii (Hance) Merr. Et

Perry & Root from Ampelopsis Sinica (Miq) W.T. Wang & Root from Ormosia Henryi Prain & Cuscuta Japonica Choisy